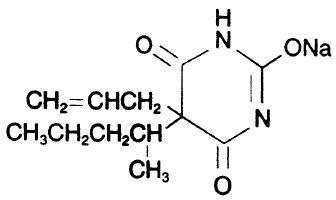 DRUG LABEL: Unknown
Manufacturer: Ranbaxy Pharmaceuticals Inc.
Category: prescription | Type: HUMAN PRESCRIPTION DRUG LABELING
Date: 20070531
DEA Schedule: CII

SECONAL SODIUM
SECOBARBITAL SODIUM CAPSULES
CII
Rx only

DESCRIPTION

The barbiturates are nonselective central nervous system (CNS) depressants that are primarily used as sedative hypnotics. In subhypnotic doses, they are also used as anticonvulsants. The barbiturates and their sodium salts are subject to control under the Federal Controlled Substances Act.

Seconal Sodium® (Secobarbital Sodium Capsules, USP) is a barbituric acid derivative and occurs as a white, odorless, bitter powder that is very soluble in water, soluble in alcohol, and practically insoluble in ether. Chemically, the drug is sodium 5-allyl-5-(1-methylbutyl) barbiturate, with the molecular formula C12H17N2NaO3. Its molecular weight is 260.27. The structural formula is as follows:

Each capsule contains 100 mg (0.38 mmol) of secobarbital sodium. It also contains dimethicone, FD&C Red No. 3, FD&C Yellow No. 10, gelatin, magnesium stearate, pregelatinized starch, and titanium dioxide.

CLINICAL PHARMACOLOGY

Barbiturates are capable of producing all levels of CNS mood alteration, from excitation to mild sedation, hypnosis, and deep coma. Overdosage can produce death. In high enough therapeutic doses, barbiturates induce anesthesia. Barbiturates depress the sensory cortex, decrease motor activity, alter cerebellar function, and produce drowsiness, sedation, and hypnosis.

Barbiturate-induced sleep differs from physiologic sleep. Sleep laboratory studies have demonstrated that barbiturates reduce the amount of time spent in the rapid eye movement (REM) phase, or dreaming stage of sleep. Also, Stages III and IV sleep are decreased. Following abrupt cessation of regularly used barbiturates, patients may experience markedly increased dreaming, nightmares, and/or insomnia. Therefore, withdrawal of a single therapeutic dose over 5 or 6 days has been recommended to lessen the REM rebound and disturbed sleep that contribute to drug withdrawal syndrome (for example, decreasing the dose from 3 to 2 doses a day for 1 week).

In studies, secobarbital sodium and pentobarbital sodium have been found to lose most of their effectiveness for both inducing and maintaining sleep by the end of 2 weeks of continued drug administration, even with the use of multiple doses. As with secobarbital sodium and pentobarbital sodium, other barbiturates (including amobarbital) might be expected to lose their effectiveness for inducing and maintaining sleep after about 2 weeks. The short-, intermediate-, and to a lesser degree, long-acting barbiturates have been widely prescribed for treating insomnia. Although the clinical literature abounds with claims that the shortacting barbiturates are superior for producing sleep whereas the intermediate-acting compounds are more effective in maintaining sleep, controlled studies have failed to demonstrate these differential effects. Therefore, as sleep medications, the barbiturates are of limited value beyond short-term use.

Barbiturates have little analgesic action at subanesthetic doses. Rather, in subanesthetic doses, these drugs may increase the reaction to painful stimuli. All barbiturates exhibit anticonvulsant activity in anesthetic doses. However, of the drugs in this class, only phenobarbital, mephobarbital, and metharbital are effective as oral anticonvulsants in subhypnotic doses.

Barbiturates are respiratory depressants, and the degree of depression is dependent on the dose. With hypnotic doses, respiratory depression is similar to that which occurs during physiologic sleep accompanied by a slight decrease in blood pressure and heart rate.

Studies in laboratory animals have shown that barbiturates cause reduction in the tone and contractility of the uterus, ureters, and urinary bladder. However, concentrations of the drugs required to produce this effect in humans are not reached with sedative-hypnotic doses.

Barbiturates do not impair normal hepatic function, but have been shown to induce liver microsomal enzymes, thus increasing and/or altering the metabolism of barbiturates and other drugs (see Drug Interactions under Precautions).

Pharmacokinetics

Barbiturates are absorbed in varying degrees following oral or parenteral administration. The salts are more rapidly absorbed than are the acids. The rate of absorption is increased if the sodium salt is ingested as a dilute solution or taken on an empty stomach.

Duration of action, which is related to the rate at which the barbiturates are redistributed throughout the body, varies among persons and in the same person from time to time.

Seconal Sodium is classified as a short-acting barbiturate when taken orally. Its onset of action is 10 to 15 minutes and its duration of action ranges from 3 to 4 hours.

Barbiturates are weak acids that are absorbed and rapidly distributed to all tissues and fluids, with high concentrations in the brain, liver, and kidneys. Lipid solubility of the barbiturates is the dominant factor in their distribution within the body. The more lipid soluble the barbiturate, the more rapidly it penetrates all tissues of the body. Barbiturates are bound to plasma and tissue proteins to a varying degree, with the degree of binding increasing directly as a function of lipid solubility.

Phenobarbital has the lowest lipid solubility, lowest plasma binding, lowest brain protein binding, the longest delay in onset of activity, and the longest duration of action. At the opposite extreme is secobarbital, which has the highest lipid solubility, highest plasma protein binding, highest brain protein binding, the shortest delay in onset of activity, and the shortest duration of action. The plasma half-life for secobarbital sodium in adults ranges between 15 to 40 hours, with a mean of 28 hours. No data are available for pediatric patients and newborns.

Barbiturates are metabolized primarily by the hepatic microsomal enzyme system, and the metabolic products are excreted in the urine and, less commonly, in the feces. The excretion of unmetabolized barbiturate is 1 feature that distinguishes the long-acting category from those belonging to other categories, which are almost entirely metabolized. The inactive metabolites of the barbiturates are excreted as conjugates of glucuronic acid.

INDICATIONS AND USAGE

A. Hypnotic, for the short-term treatment of insomnia, since it appears to lose its effectiveness for sleep induction and sleep maintenance after 2 weeks (see Clinical Pharmacology).

B. Preanesthetic

CONTRAINDICATIONS

Seconal Sodium is contraindicated in patients who are hypersensitive to barbiturates. It is also contraindicated in patients with a history of manifest or latent porphyria, marked impairment of liver function, or respiratory disease in which dyspnea or obstruction is evident.

WARNINGS

Because sleep disturbances may be the presenting manifestation of a physical and/or psychiatric disorder, symptomatic treatment of insomnia should be initiated only after a careful evaluation of the patient. The failure of insomnia to remit after 7 to 10 days of treatment may indicate the presence of a primary psychiatric and/or medical illness that should be evaluated. Worsening of insomnia or the emergence of new thinking or behavior abnormalities may be the consequence of an unrecognized psychiatric or physical disorder. Such findings have emerged during the course of treatment with sedative-hypnotic drugs. Because some of the important adverse effects of sedative-hypnotics appear to be dose related (see Precautions and Dosage and Administration), it is important to use the smallest possible effective dose, especially in the elderly.

Complex behaviors such as “sleep-driving” (i.e., driving while not fully awake after ingestion of a sedative-hypnotic, with amnesia for the event) have been reported. These events can occur in sedative-hypnotic-naïve as well as in sedative-hypnotic-experienced persons. Although behaviors such as sleep-driving may occur with sedative-hypnotics alone at therapeutic doses, the use of alcohol and other CNS depressants with sedative-hypnotics appears to increase the risk of such behaviors, as does the use of sedative-hypnotics at doses exceeding the maximum recommended dose. Due to the risk to the patient and the community, discontinuation of sedative-hypnotics should be strongly considered for patients who report a “sleep-driving” episode.

Other complex behaviors (e.g., preparing and eating food, making phone calls, or having sex) have been reported in patients who are not fully awake after taking a sedative-hypnotic. As with sleep-driving, patients usually do not remember these events.

1. Habit-Forming—Seconal Sodium may be habit-forming. Tolerance and psychological and physical dependence may occur with continued use (see Drug Abuse and Dependence and Pharmacokinetics under Clinical Pharmacology). Patients who have psychological dependence on barbiturates may increase the dosage or decrease the dosage interval without consulting a physician and subsequently may develop a physical dependence on barbiturates. To minimize the possibility of overdosage or development of dependence, the prescribing and dispensing of sedative-hypnotic barbiturates should be limited to the amount required for the interval until the next appointment. The abrupt cessation after prolonged use in a person who is dependent on the drug may result in withdrawal symptoms, including delirium, convulsions, and possibly death. Barbiturates should be withdrawn gradually from any patient known to be taking excessive doses over long periods of time (see Drug Abuse and Dependence).

2. Acute or Chronic Pain—Caution should be exercised when barbiturates are administered to patients with acute or chronic pain, because paradoxical excitement could be induced or important symptoms could be masked.

3. Usage in Pregnancy—Barbiturates can cause fetal harm when administered to a pregnant woman. Retrospective, case-controlled studies have suggested that there may be a connection between the maternal consumption of barbiturates and a higher than expected incidence of fetal abnormalities. Barbiturates readily cross the placental barrier and are distributed throughout fetal tissues; the highest concentrations are found in the placenta, fetal liver, and brain. Fetal blood levels approach maternal blood levels following parenteral administration.

Withdrawal symptoms occur in infants born to women who receive barbiturates throughout the last trimester of pregnancy (see Drug Abuse and Dependence). If Seconal Sodium is used during pregnancy or if the patient becomes pregnant while taking this drug, the patient should be apprised of the potential hazard to the fetus.

4. Synergistic Effects—The concomitant use of alcohol or other CNS depressants may produce additive CNS-depressant effects.

PRECAUTIONS

General

Barbiturates may be habit-forming. Tolerance and psychological and physical dependence may occur with continuing use (see Drug Abuse and Dependence). Barbiturates should be administered with caution, if at all, to patients who are mentally depressed, have suicidal tendencies, or have a history of drug abuse.

Elderly or debilitated patients may react to barbiturates with marked excitement, depression, or confusion. In some persons, especially pediatric patients, barbiturates repeatedly produce excitement rather than depression.

In patients with hepatic damage, barbiturates should be administered with caution and initially in reduced doses. Barbiturates should not be administered to patients showing the premonitory signs of hepatic coma.

Information for Patients

“Sleep-Driving” and other complex behaviors:

There have been reports of people getting out of bed after taking a sedative-hypnotic and driving their cars while not fully awake, often with no memory of the event. If a patient experiences such an episode, it should be reported to his or her doctor immediately, since “sleep-driving” can be dangerous. This behavior is more likely to occur when sedative-hypnotics are taken with alcohol or other central nervous system depressants (see WARNINGS). Other complex behaviors (e.g., preparing and eating food, making phone calls, or having sex) have been reported in patients who are not fully awake after taking a sedative-hypnotic. As with sleep-driving, patients usually do not remember these events.

The following information should be given to patients receiving Seconal Sodium:

1. The use of Seconal Sodium carries with it an associated risk of psychological and/or physical dependence. The patient should be warned against increasing the dose of the drug without consulting a physician.

2. Seconal Sodium may impair the mental and/or physical abilities required for the performance of potentially hazardous tasks, such as driving a car or operating machinery. The patient should be cautioned accordingly.

3. Alcohol should not be consumed while taking Seconal Sodium. The concurrent use of Seconal Sodium with other CNS depressants (eg, alcohol, narcotics, tranquilizers, and antihistamines) may result in additional CNS-depressant effects.

Laboratory Tests

Prolonged therapy with barbiturates should be accompanied by periodic laboratory evaluation of organic systems, including hematopoietic, renal, and hepatic systems (see General under Precautions and Adverse Reactions).

Drug Interactions

Most reports of clinically significant drug interactions occurring with the barbiturates have involved phenobarbital. However, the application of these data to other barbiturates appears valid and warrants serial blood level determinations of the relevant drugs when there are multiple therapies.

1. Anticoagulants—Phenobarbital lowers the plasma levels of dicumarol and causes a decrease in anticoagulant activity as measured by the prothrombin time. Barbiturates can induce hepatic microsomal enzymes, resulting in increased metabolism and decreased anticoagulant response of oral anticoagulants (eg, warfarin, acenocoumarol, dicumarol, and phenprocoumon). Patients stabilized on anticoagulant therapy may require dosage adjustments if barbiturates are added to or withdrawn from their dosage regimen.

2. Corticosteroids—Barbiturates appear to enhance the metabolism of exogenous corticosteroids, probably through the induction of hepatic microsomal enzymes. Patients stabilized on corticosteroid therapy may require dosage adjustments if barbiturates are added to or withdrawn from their dosage regimen.

3. Griseofulvin—Phenobarbital appears to interfere with the absorption of orally administered griseofulvin, thus decreasing its blood level. The effect of the resultant decreased blood levels of griseofulvin on therapeutic response has not been established. However, it would be preferable to avoid concomitant administration of these drugs.

4. Doxycycline—Phenobarbital has been shown to shorten the half-life of doxycycline for as long as 2 weeks after barbiturate therapy is discontinued.

This mechanism is probably through the induction of hepatic microsomal enzymes that metabolize the antibiotic. If barbiturates and doxycycline are administered concurrently, the clinical response to doxycycline should be monitored closely.

5. Phenytoin, Sodium Valproate, Valproic Acid—The effect of barbiturates on the metabolism of phenytoin appears to be variable. Some investigators report an accelerating effect, whereas others report no effect. Because the effect of barbiturates on the metabolism of phenytoin is not predictable, phenytoin and barbiturate blood levels should be monitored more frequently if these drugs are given concurrently. Sodium valproate and valproic acid increase the secobarbital sodium serum levels; therefore, secobarbital sodium blood levels should be monitored closely and appropriate dosage adjustments made as clinically indicated.

6. CNS Depressants—The concomitant use of other CNS depressants, including other sedatives or hypnotics, antihistamines, tranquilizers, or alcohol, may produce additive depressant effects.

7. Monoamine Oxidase Inhibitors (MAOIs)—MAOIs prolong the effects of barbiturates, probably because metabolism of the barbiturate is inhibited.

8. Estradiol, Estrone, Progesterone, and Other Steroidal Hormones—Pretreatment with or concurrent administration of phenobarbital may decrease the effect of estradiol by increasing its metabolism. There have been reports of patients treated with antiepileptic drugs (eg, phenobarbital) who become pregnant while taking oral contraceptives. An alternate contraceptive method might be suggested to women taking barbiturates.

Carcinogenesis

1. Animal Data. Phenobarbital sodium is carcinogenic in mice and rats after lifetime administration. In mice, it produced benign and malignant liver cell tumors. In rats, benign liver cell tumors were observed very late in life.

2. Human Data—In a 29-year epidemiologic study of 9,136 patients who were treated on an anticonvulsant protocol that included phenobarbital, results indicated a higher than normal incidence of hepatic carcinoma. Previously, some of these patients had been treated with thorotrast, a drug that is known to produce hepatic carcinomas. Thus, this study did not provide sufficient evidence that phenobarbital sodium is carcinogenic in humans.

A retrospective study of 84 pediatric patients with brain tumors matched to 73 normal controls and 78 cancer controls (malignant disease other than brain tumors) suggested an association between exposure to barbiturates prenatally and an increased incidence of brain tumors.

Usage in pregnancy

1. Teratogenic Effects

Pregnancy Category D. See Usage in Pregnancy under Warnings.

2. Nonteratogenic Effects

Reports of infants suffering from long-term barbiturate exposure in utero included the acute withdrawal syndrome of seizures and hyperirritability from birth to a delayed onset of up to 14 days (see Drug Abuse and Dependence).

Labor and Delivery

Hypnotic doses of barbiturates do not appear to impair uterine activity significantly during labor. Full anesthetic doses of barbiturates decrease the force and frequency of uterine contractions. Administration of sedative-hypnotic barbiturates to the mother during labor may result in respiratory depression in the newborn. Premature infants are particularly susceptible to the depressant effects of barbiturates. If barbiturates are used during labor and delivery, resuscitation equipment should be available.

Data are not available to evaluate the effect of barbiturates when forceps delivery or other intervention is necessary or to determine the effect of barbiturates on the later growth, development, and functional maturity of the pediatric patient.

Nursing Mothers

Caution should be exercised when Seconal Sodium is administered to a nursing woman, because small amounts of barbiturates are excreted in the milk.

ADVERSE REACTIONS

The following adverse reactions and their incidences were compiled from surveillance of thousands of hospitalized patients who received barbiturates. Because such patients may be less aware of some of the milder adverse effects of barbiturates, the incidence of these reactions may be somewhat higher in fully ambulatory patients.

More than 1 in 100 Patients

The most common adverse reaction estimated to occur at a rate of 1 to 3 patients per 100 is the following:

Nervous System: Somnolence

Less than 1 in 100 Patients

Adverse reactions estimated to occur at a rate of less than 1 in 100 patients are listed below, grouped by organ system and by decreasing order of occurrence:

Nervous System: Agitation, confusion, hyperkinesia, ataxia, CNS depression, nightmares, nervousness, psychiatric disturbance, hallucinations, insomnia, anxiety, dizziness, abnormality in thinking

Respiratory System: Hypoventilation, apnea

Cardiovascular System: Bradycardia, hypotension, syncope

Digestive System: Nausea, vomiting, constipation

Other Reported Reactions: Headache, injection site reactions, hypersensitivity reactions (angioedema, skin rashes, exfoliative dermatitis), fever, liver damage, megaloblastic anemia following chronic phenobarbital use

DRUG ABUSE AND DEPENDENCE

Abuse and addiction are separate and distinct from physical dependence and tolerance. Abuse is characterized by misuse of the drug for non-medical purposes, often in combination with other psychoactive substances. Physical dependence is a state of adaptation that is manifested by a specific withdrawal syndrome that can be produced by abrupt cessation, rapid dose reduction, decreasing blood level of the drug and/or administration of an antagonist. Tolerance is a state of adaptation in which exposure to a drug induces changes that result in a diminution of one or more of the drug’s effects over time. Tolerance may occur to both the desired and undesired effects of drugs and may develop at different rates for different effects.

Addiction is primary, chronic, neurobiological disease with genetic, psychosocial, and environmental factors influencing its development and manifestations. It is characterized by behaviors that include one or more of the following: impaired control over drug use, compulsive use, continued use despite harm, and craving. Drug addiction is a treatable disease, utilizing a multidisciplinary approach, but relapse is common.

Controlled substance─ Seconal Sodium Capsules are a Schedule II drug.

Dependence─ Barbiturates may be habit-forming; tolerance, psychological dependence, and physical dependence may occur, especially following prolonged use of high doses of barbiturates. Daily administration in excess of 400 mg of secobarbital for approximately 90 days is likely to produce some degree of physical dependence. A dosage of 600 to 800 mg for at least 35 days is sufficient to produce withdrawal seizures. The average daily dose for the barbiturate addict is usually about 1.5 g. As tolerance to barbiturates develops, the amount needed to maintain the same level of intoxication increases; tolerance to a fatal dosage, however, does not increase more than twofold. As this occurs, the margin between intoxicating dosage and fatal dosage becomes smaller.

Symptoms of acute intoxication with barbiturates include unsteady gait, slurred speech, and sustained nystagmus. Mental signs of chronic intoxication include confusion, poor judgment, irritability, insomnia, and somatic complaints.

Symptoms of barbiturate dependence are similar to those of chronic alcoholism. If an individual appears to be intoxicated with alcohol to a degree that is radically disproportionate to the amount of alcohol in his or her blood, the use of barbiturates should be suspected. The lethal dose of a barbiturate is far less if alcohol is also ingested.

The symptoms of barbiturate withdrawal can be severe and may cause death. Minor withdrawal symptoms may appear 8 to 12 hours after the last dose of a barbiturate. These symptoms usually appear in the following order: anxiety, muscle twitching, tremor of hands and fingers, progressive weakness, dizziness, distortion in visual perception, nausea, vomiting, insomnia, and orthostatic hypotension. Major withdrawal symptoms (convulsions and delirium) may occur within 16 hours and last up to 5 days after abrupt cessation of barbiturates. Intensity of withdrawal symptoms gradually declines over a period of approximately 15 days. Individuals susceptible to barbiturate abuse and dependence include alcoholics and opiate abusers, as well as other sedative-hypnotic and amphetamine abusers.

Drug dependence on barbiturates arises from repeated administration on a continuous basis, generally in amounts exceeding therapeutic dose levels. The characteristics of drug dependence on barbiturates include the following: (a) a strong desire or need to continue taking the drug; (b) a tendency to increase the dose; (c) a psychic dependence on the effects of the drug related to subjective and individual appreciation of those effects; and (d) a physical dependence on the effects of the drug, requiring its presence for maintenance of homeostasis and resulting in a definite, characteristic, and self-limited abstinence syndrome when the drug is withdrawn.

Treatment of barbiturate dependence consists of cautious and gradual withdrawal of the drug. Barbiturate-dependent patients can be withdrawn by using a number of withdrawal regimens. In all cases, withdrawal takes an extended period. One method involves substituting a 30-mg dose of phenobarbital for each 100- to 200-mg dose of barbiturate that the patient has been taking. The total daily amount of phenobarbital is then administered in 3 or 4 divided doses, not to exceed 600 mg daily. Should signs of withdrawal occur on the first day of treatment, a loading dose of 100 to 200 mg of phenobarbital may be administered IM in addition to the oral dose. After stabilization on phenobarbital, the total daily dose is decreased by 30 mg a day as long as withdrawal is proceeding smoothly. A modification of this regimen involves initiating treatment at the patient’s regular dosage level and decreasing the daily dosage by 10% as tolerated by the patient.

Infants that are physically dependent on barbiturates may be given phenobarbital, 3 to 10 mg/kg/day. After withdrawal symptoms (hyperactivity, disturbed sleep, tremors, and hyperreflexia) are relieved, the dosage of phenobarbital should be gradually decreased and completely withdrawn over a 2-week period.

OVERDOSAGE

The toxic dose of barbiturates varies considerably. In general, an oral dose of 1 g of most barbiturates produces serious poisoning in an adult. Death commonly occurs after 2 to 10 g of ingested barbiturate. The sedated, therapeutic blood levels of secobarbital range between 0.5 to 5 mcg/mL; the usual lethal blood level ranges from 15 to 40 mcg/mL. Barbiturate intoxication may be confused with alcoholism, bromide intoxication, and various neurologic disorders. Potential tolerance must be considered when evaluating significance of dose and plasma concentration.

Signs and Symptoms—Symptoms of oral overdose may occur within 15 minutes and begin with central nervous system depression, underventilation, hypotension, and hypothermia, which may progress to pulmonary edema and death. Hemorrhagic blisters may develop, especially at pressure points.

In extreme overdose, all electrical activity in the brain may cease, in which case a “flat” EEG normally equated with clinical death cannot be accepted as indicative of brain death. This effect is fully reversible unless hypoxic damage occurs. Consideration should be given to the possibility of barbiturate intoxication even in situations that appear to involve trauma.

Complications such as pneumonia, pulmonary edema, cardiac arrhythmias, congestive heart failure, and renal failure may occur. Uremia may increase CNS sensitivity to barbiturates if renal function is impaired. Differential diagnosis should include hypoglycemia, head trauma, cerebrovascular accidents, convulsive states, and diabetic coma.

Treatment—To obtain up-to-date information about the treatment of overdose, a good resource is your certified Regional Poison Control Center. Telephone numbers of certified poison control centers are listed in the Physicians’ Desk Reference (PDR). In managing overdosage, consider the possibility of multiple drug overdoses, interaction among drugs, and unusual drug kinetics in your patient.

Protect the patient’s airway and support ventilation and perfusion. Meticulously monitor and maintain, within acceptable limits, the patient’s vital signs, blood gases, serum electrolytes, etc. Absorption of drugs from the gastrointestinal tract may be decreased by giving activated charcoal, which, in many cases, is more effective than emesis or lavage; consider charcoal instead of or in addition to gastric emptying. Repeated doses of charcoal over time may hasten elimination of some drugs that have been absorbed. Safeguard the patient’s airway when employing gastric emptying or charcoal.

Diuresis and peritoneal dialysis are of little value; hemodialysis and hemoperfusion enhance drug clearance and should be considered in serious poisoning. If the patient has chronically abused sedatives, withdrawal reactions may be manifest following acute overdose.

DOSAGE AND ADMINISTRATION

Dosages of barbiturates must be individualized with full knowledge of their particular characteristics. Factors of consideration are the patient’s age, weight, and condition.

Adults—As a hypnotic, 100 mg at bedtime. Preoperatively, 200 to 300 mg 1 to 2 hours before surgery.

Pediatric Patients—Preoperatively, 2 to 6 mg/kg, with a maximum dosage of 100 mg.

Special patient population—Dosage should be reduced in the elderly or debilitated because these patients may be more sensitive to barbiturates. Dosage should be reduced for patients with impaired renal function or hepatic disease.

HOW SUPPLIED

Seconal Sodium capsules are (orange) and imprinted with RX679 on both the cap and the body:

NDC 63304-679-01 100 mg Bottles of 100

Store at 20 - 25° C (68 - 77° F). (See USP Controlled Room Temperature). Dispense in a tight container.

Manufactured for:

Ranbaxy Pharmaceuticals Inc.

Jacksonville, FL 32257 USA

by: Ohm Laboratories, Inc.

North Brunswick, NJ 08902 USA

May 2007